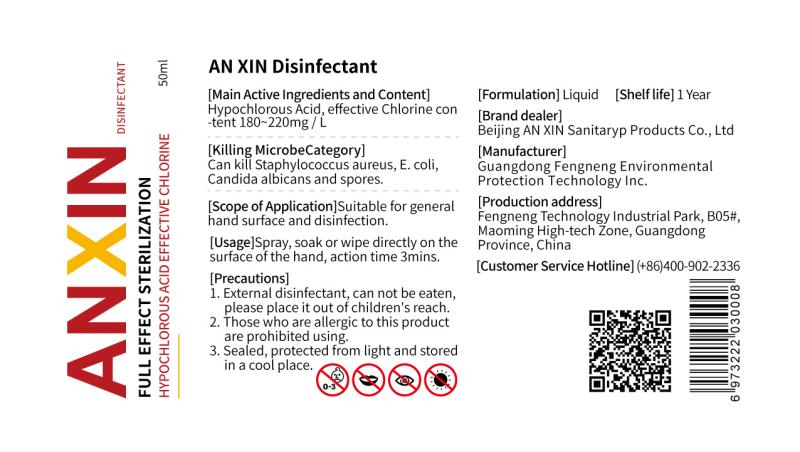 DRUG LABEL: AN XIN Disinfectant
NDC: 56114-001 | Form: LIQUID
Manufacturer: Guangdong Fengneng Environmental Protection Technology Inc.
Category: otc | Type: HUMAN OTC DRUG LABEL
Date: 20200618

ACTIVE INGREDIENTS: HYPOCHLOROUS ACID 10 mg/50 mL
INACTIVE INGREDIENTS: WATER

DOSAGE AND ADMINISTRATION

Sealed, protected from light and stored in a cool place.

INACTIVE INGREDIENT

Water

INDICATIONS AND USAGE

Spray, soak or wipe directly on the surface of the hand, action time 3mins.

ACTIVE INGREDIENT

Hypochlorous acid

keep out of reach of children

PURPOSE

Disinfection
Sterilization

WARNINGS

1. External disinfectant, can not be eaten,please place it out of children's reach.
2. Those who are allergic to this product are prohibited using.
3. Sealed, protected from light and stored in a cool place.